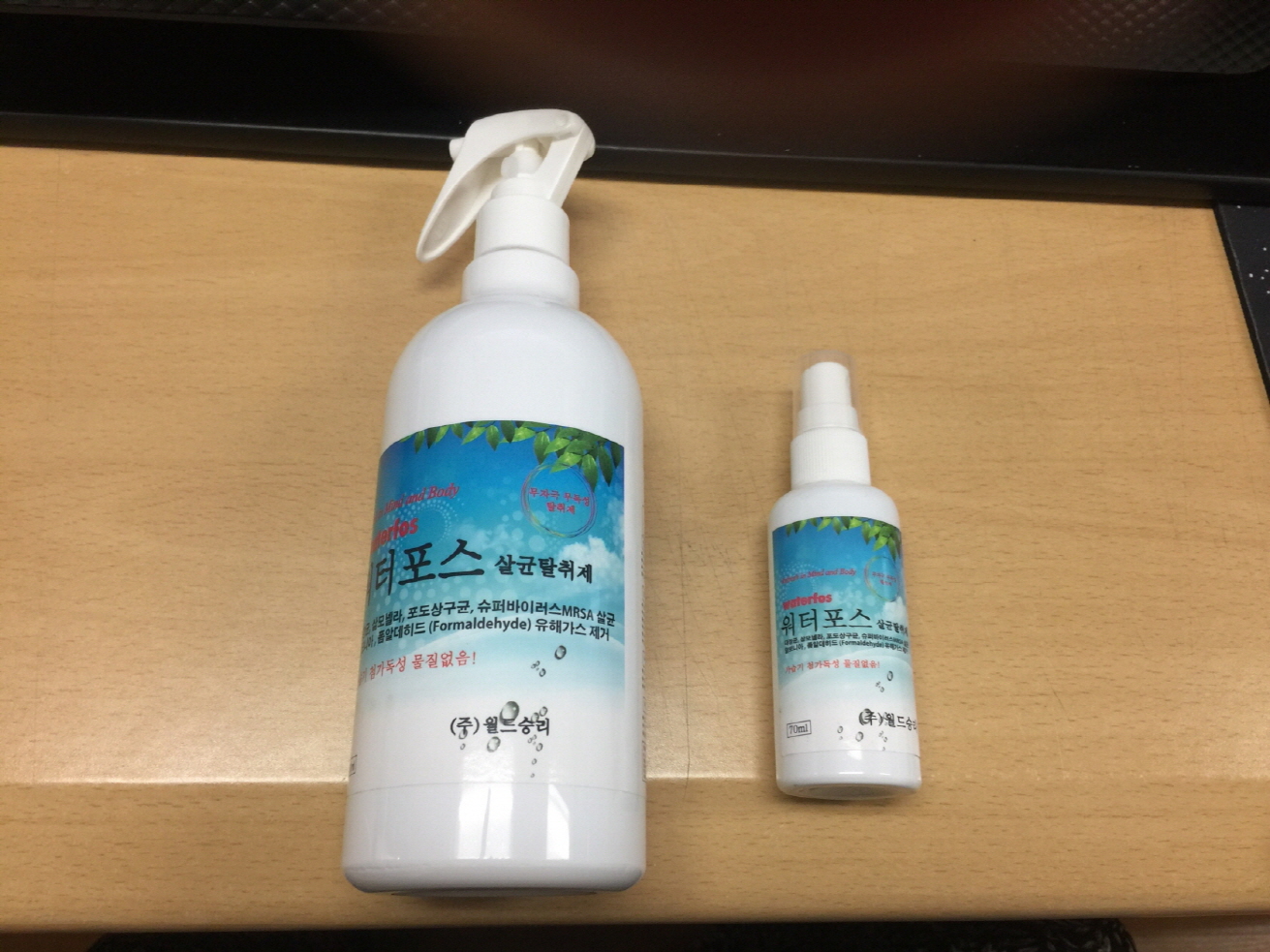 DRUG LABEL: Disinfectant Deodorant (Waterfos)
NDC: 71587-0001 | Form: LIQUID
Manufacturer: World Sung Ri Co., Ltd
Category: otc | Type: HUMAN OTC DRUG LABEL
Date: 20191231

ACTIVE INGREDIENTS: OSTREA EDULIS SHELL 20 g/100 mL; SILVER 0.01 g/100 mL
INACTIVE INGREDIENTS: FERRIC CHLORIDE; GERMANIUM; WATER

Active ingredient

oystershell 20%, nano silver 0.01%

Purpose

Disinfectant Deodorant

Use

-For indoors and air: spray the product evenly over the odor causing area, and be careful

not to slip

-For clothes: From a distance of 20-40cm, spray evenly on the desired area

-For wallpaper: From a distance of 30cm, spray evenly to prevent crumpling

WARNINGS

-Although safe to the eyes and skin, upon contact wash with clean water

-Do not store in direct sunlight or in areas of temperatures in excess of 40 degrees C.

-Use the product only for intended purposes.

Keep out of reach of children

Directions

For external use only

INACTIVE INGREDIENT

barley stone, zeolite, germanium, ferric chloride, sugar, additive, distilled water